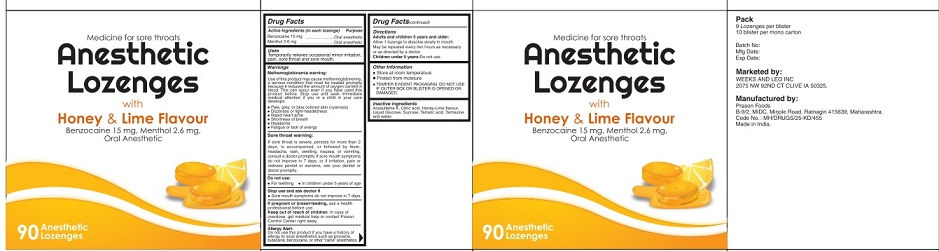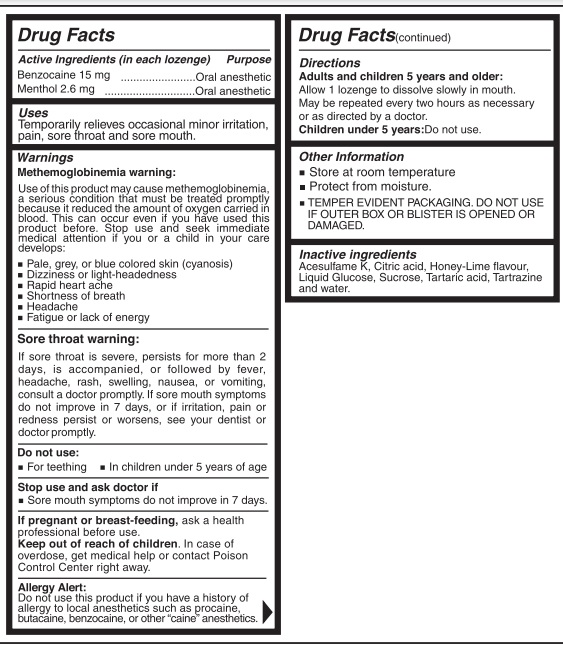 DRUG LABEL: Anesthetic Lozenges Honey Lime Flavors
NDC: 83348-002 | Form: LOZENGE
Manufacturer: PRASON FOODS
Category: otc | Type: HUMAN OTC DRUG LABEL
Date: 20230502

ACTIVE INGREDIENTS: BENZOCAINE 15 mg/1 1; MENTHOL 2.6 mg/1 1
INACTIVE INGREDIENTS: DEXTROSE, UNSPECIFIED FORM; SUCROSE; ACESULFAME POTASSIUM; TARTARIC ACID; CITRIC ACID MONOHYDRATE; FD&C YELLOW NO. 5; WATER

Active Ingredient

Benzocaine 15 mg

Menthol 2.6 mg

Purpose

Oral anesthetic

Uses

Temporarily relieves occasional minor irritation, pain, sore throat and sore mouth.

Warning

Methemoglobinemia warning
Use of this product may cause methemoglobinemia, a serious condition that must be treated promptly because it reduced the amount of oxygen carried in blood. This can occur even if you have used this product before. Stop use and seek immediate medical attention if you or a child in your care develops

- Pale, grey, or blue colored skin (Cyanosis)
- Headache
- Rapid heart ache
- Shortness of breath
- Dizziness or light headedness
- Fatigue or lack of energy

Sore throat warning

If sore throat is severe, persists for more than 2 days, is accompanied, or followed by fever, headache, rash, swelling, nausea, or vomiting, consult a doctor promptly. If sore mouth symptoms do not improve in 7 days, or if irritation, pain or redness persist or worsens, see your dentist or doctor promptly.

Do not use

- For teething
- In children under 5 years of age

Stop use and ask doctor if

- Sore mouth symptoms do not improve in 7 days.

If pregnant or breast-feeding, ask a health professional before use.

Keep out of reach of children. In case of overdose, get medical help or contact Poison Control Center right away.

Allergy alert : Do not use this product if you have a history of allergy to local anesthetic such as procaine, butacaine, benzocaine, or other "caine" anesthetics

Directions

Adults and children 5 years and older:

Allow 1 lozenge to dissolve slowly in mouth. May be repeated every two hours as necessary or as directed by a doctor.

Children under 5 years: Do not use.

Other Information

- Store at room temperature
- Protect from moisture.

TEMPER EVIDENT PACKAGING. DO NOT USE IF OUTER BOX OR BLISTER IS OPENED OR DAMAGED.

Inactive ingredients

Acesulfame k, Citric acid, Honey lime flavor, Liquid glucose, Sucrose, Tartaric acid, Tartrazine and Water